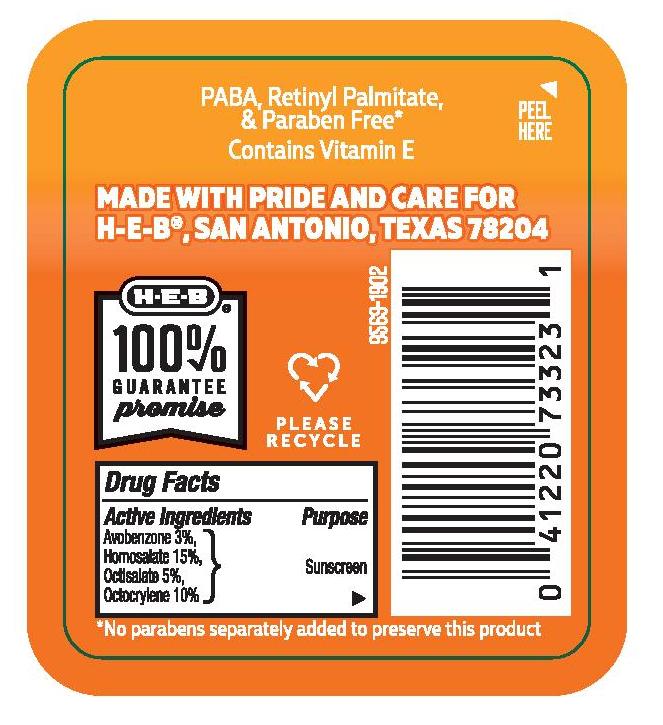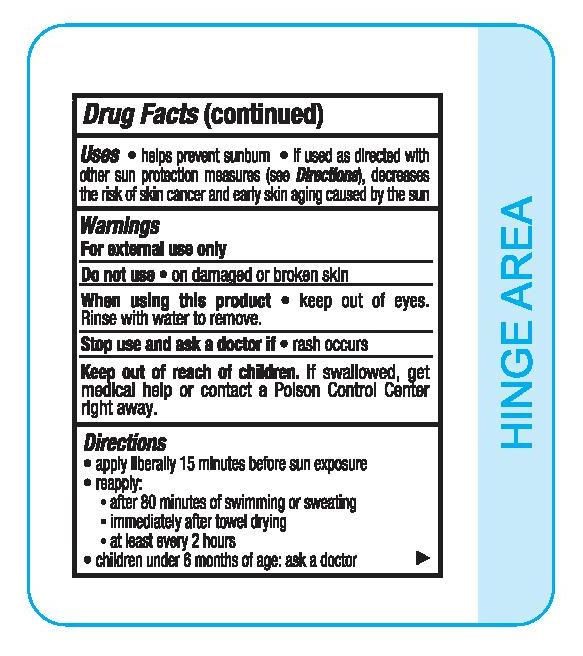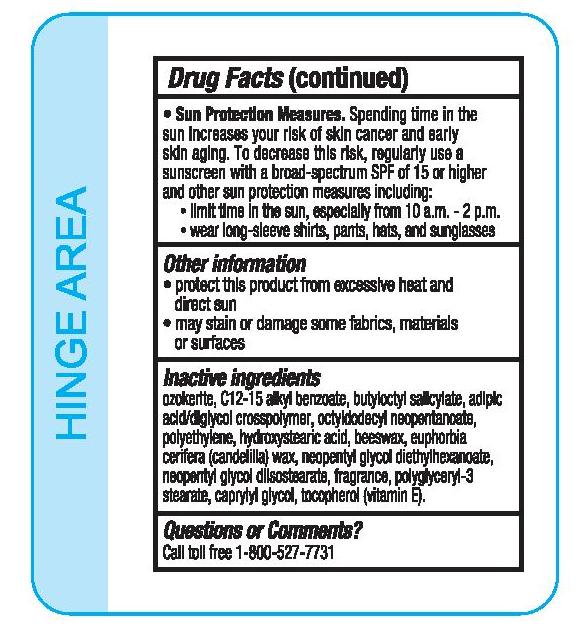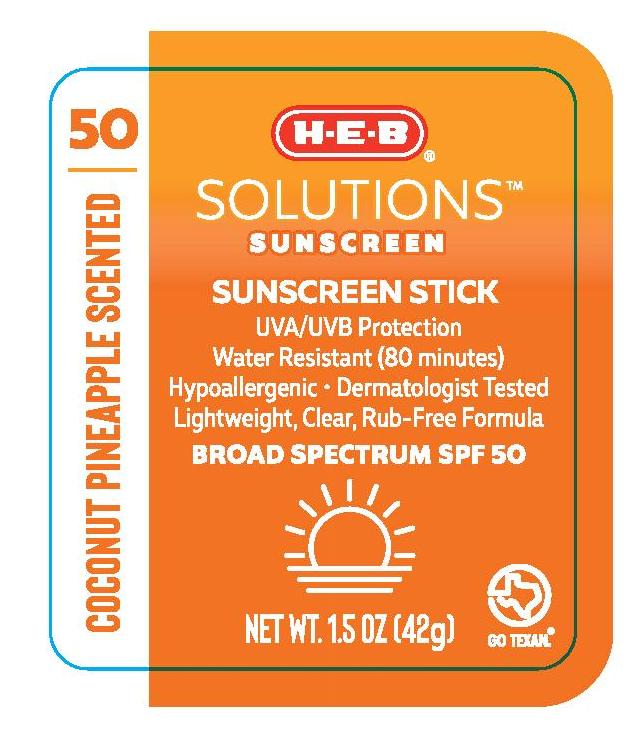 DRUG LABEL: H.E.B
NDC: 37808-962 | Form: STICK
Manufacturer: H.E.B
Category: otc | Type: HUMAN OTC DRUG LABEL
Date: 20210709

ACTIVE INGREDIENTS: AVOBENZONE 30 mg/1 g; HOMOSALATE 150 mg/1 g; OCTISALATE 50 mg/1 g; OCTOCRYLENE 100 mg/1 g
INACTIVE INGREDIENTS: ADIPIC ACID/DIGLYCOL CROSSPOLYMER (20000 MPA.S); YELLOW WAX; TOCOPHEROL; BUTYLOCTYL SALICYLATE; ALKYL (C12-15) BENZOATE; CAPRYLYL GLYCOL; NEOPENTYL GLYCOL DIETHYLHEXANOATE; OCTYLDODECYL NEOPENTANOATE; CERESIN; CANDELILLA WAX; HIGH DENSITY POLYETHYLENE; 12-HYDROXYSTEARIC ACID

H.E.B Solutions Sunscreen Coconut Pineapple Scented SPF 50 Stick

Active Ingredients

Avobenzone 3.0%, Homosalate 15.0%, Octisalate 5.0%, Octocrylene 10.0%

Purpose

Sunscreen

Uses

- helps prevent sunburn
- if used as directed with other sun protection measures (see Directions), decreases the risk of skin cancer and early skin aging caused by the sun

Warnings

For external use only

Do not use • on damaged or broken skin

When using this product • keep out of eyes. Rinse with water to remove.

Stop use and ask a doctor if • rash occurs

Keep out of reach of children. If swallowed, get medical help or contact a Poison Control Center right away.

Directions

- apply liberally 15 minutes before sun exposure
- reapply:

• after 80 minutes of swimming or sweating

• immediately after towel drying

• at least every 2 hours

- children under 6 months of age: ask a doctor
- Sun Protection Measures. Spending time in the sun increases your risk of skin cancer and early skin aging. To decrease this risk, regularly use a sunscreen with a broad-spectrum SPF of 15 or higher and other sun protection measures including:

• limit time in the sun, especially from 10 a.m. - 2 p.m.

• wear long-sleeve shirts, pants, hats, and sunglasses

Other information

- protect this product from excessive heat and direct sun
- may stain or damage some fabrics, materials or surfaces

Inactive ingredients

ozokerite, C12-15 alkyl benzoate, butyloctyl salicylate, adipic acid/diglycol crosspolymer, octyldodecyl neopentanoate, polyethylene, hydroxystearic acid, beeswax, euphorbia cerifera (candelilla) wax, neopentyl glycol diethylhexanoate, neopentyl glycol diisostearate, fragrance, polyglyceryl-3 stearate, caprylyl glycol, tocopherol (vitamin E).

Questions or Comments?

Call toll free 1-800-527-7731

PACKAGE LABEL

H.E.B Solutions Sunscreen Coconut Pineapple Scented SPF 50 Stick

1.5 OZ (42g)

NDC 37808-962-28